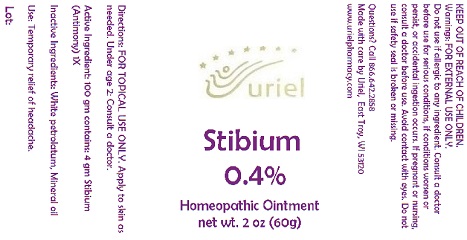 DRUG LABEL: Stibium 0.4
NDC: 48951-8225 | Form: OINTMENT
Manufacturer: Uriel Pharmacy Inc.
Category: homeopathic | Type: HUMAN OTC DRUG LABEL
Date: 20170829

ACTIVE INGREDIENTS: ANTIMONY 1 [hp_X]/1 g
INACTIVE INGREDIENTS: PETROLATUM; MINERAL OIL

Stibium 0.4

INDICATIONS AND USAGE

Directions: FOR TOPICAL USE ONLY.

DOSAGE AND ADMINISTRATION

Apply to skin as needed. Under age 2: Consult a doctor.

Active Ingredient: 100 gm contains: 4 gm Stibium (Antimony) 1X

Inactive Ingredients: White petrolatum, Mineral oil

PURPOSE

Use: Temporary relief of headache.

KEEP OUT OF REACH OF CHILDREN.

WARNINGS

Warnings: FOR EXTERNAL USE ONLY. Do not use if allergic to any ingredient. Consult a doctor before use for serious conditions, if conditions worsen or persist, or accidental ingestion occurs. If pregnant or nursing, consult a doctor before use. Avoid contact with eyes. Do not use if safety seal is broken or missing.

QUESTIONS

Questions? Call 866.642.2858 Made with care by Uriel, East Troy, WI 53120 www.urielpharmacy.com